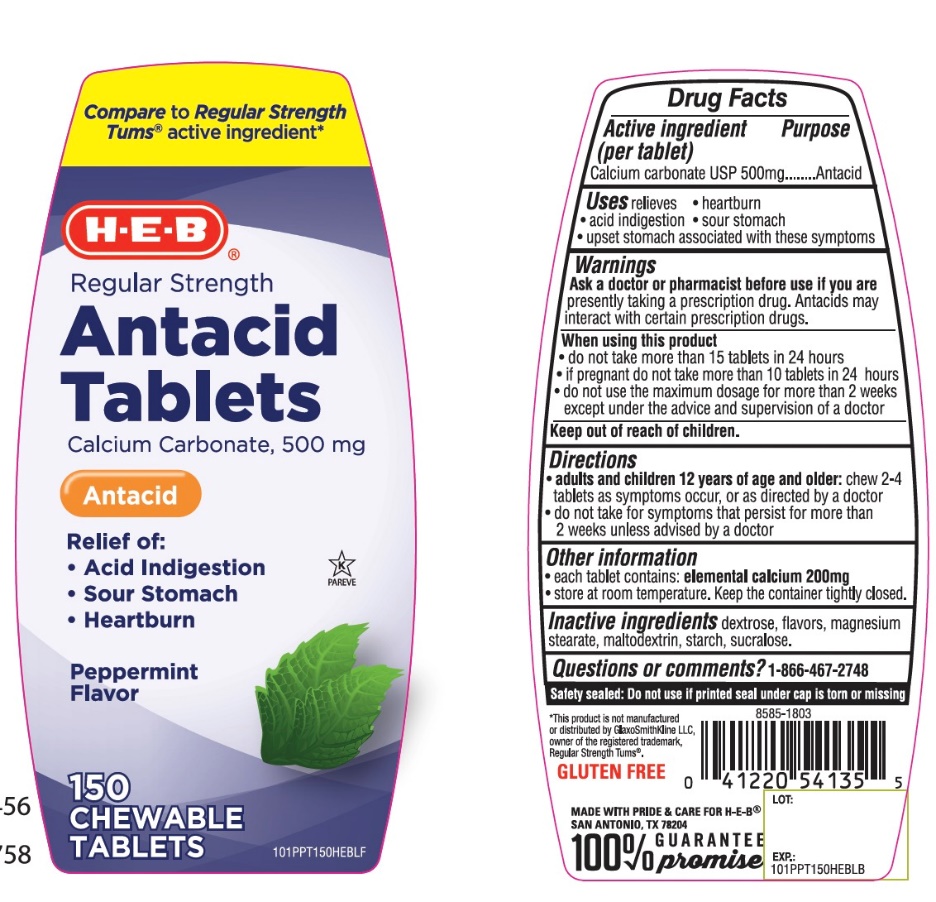 DRUG LABEL: HEB Regular Strength

NDC: 37808-111 | Form: TABLET, CHEWABLE
Manufacturer: HEB
Category: otc | Type: HUMAN OTC DRUG LABEL
Date: 20251003

ACTIVE INGREDIENTS: CALCIUM CARBONATE 500 mg/1 1
INACTIVE INGREDIENTS: DEXTROSE, UNSPECIFIED FORM; MAGNESIUM STEARATE; MALTODEXTRIN; STARCH, CORN; SUCRALOSE

H-E-B Regular Strength Antacid Calcium Carbonate Chewable Tablets 150 Count

Active ingredient (per tablet)

Calcium Carbonate USP 500mg

Purpose

Antacid

Uses

relieves

• heartburn

• acid indigestion

• sour stomach

• upset stomach associated with these symptoms

Warnings

Ask a doctor or pharmacist before use if you arepresently taking a prescription drug. Antacids may interact with certain prescription drugs.

When using this product

- do not take more than 15 tablets in 24 hours
- if pregnant do not take more than 10 tablets in 24 hours
- do not use the maximum dosage for more than 2 weeks except under the advice and supervision of a doctor.

Directions

- adults and children 12 years of age and older:chew 2-4 tablets as symptoms occur, or as directed by a doctor
- do not take for symptoms that persist for more than 2 weeks unless advised by a doctor

Other information

- each tablet contains:elemental calcium 200 mg
- store at room temperature. Keep the container tightly closed.

Inactive ingredients

dextrose, flavors, magnesium stearate, maltodextrin, starch, sucralose

Questions?

1-888-287-1915

SAFETY SEALED: DO NOT USE IF PRINTED SEAL UNDER CAP IS TORN OR MISSING

Package/Label Principal Display Panel

NDC 37808-111-15

Compare to Regular Strength Tum® Active Ingredient*

H-E-B®

Regular Strength

Antacid Tablets

Calcium Carbonate 500mg/Antacid

Fast Relief of:

- Acid indigestion
- Sour stomach
- Heartburn

Peppermint Flavor

150 CHEWABLE TABLETS

K PAREVE

GLUTEN-FREE

MADE WITH PRIDE & CARE FOR H-E-B

SAN ANTONIO, TX 78204

100% GUARANTEE promise

*This product is not manufactured or distributed by GlaxoSmithKline LLC, owner of the registered trademark, Tums®.